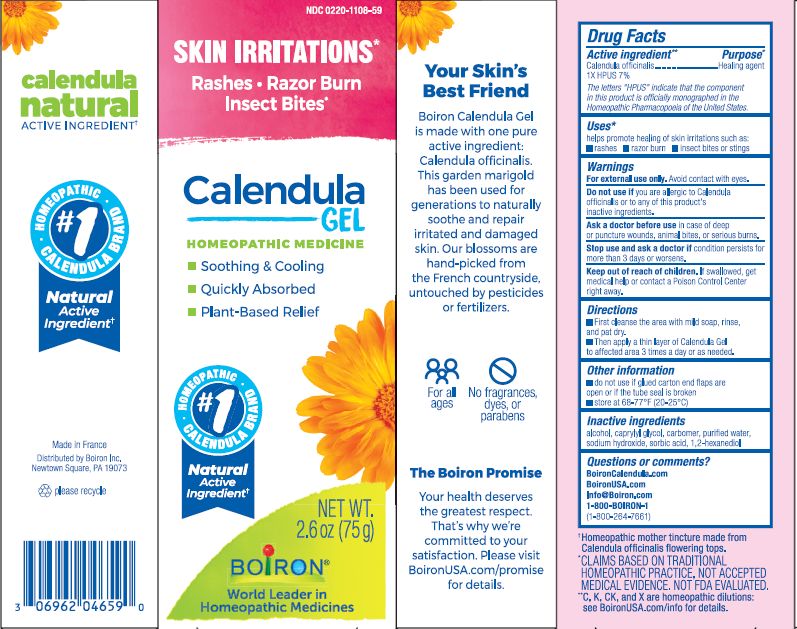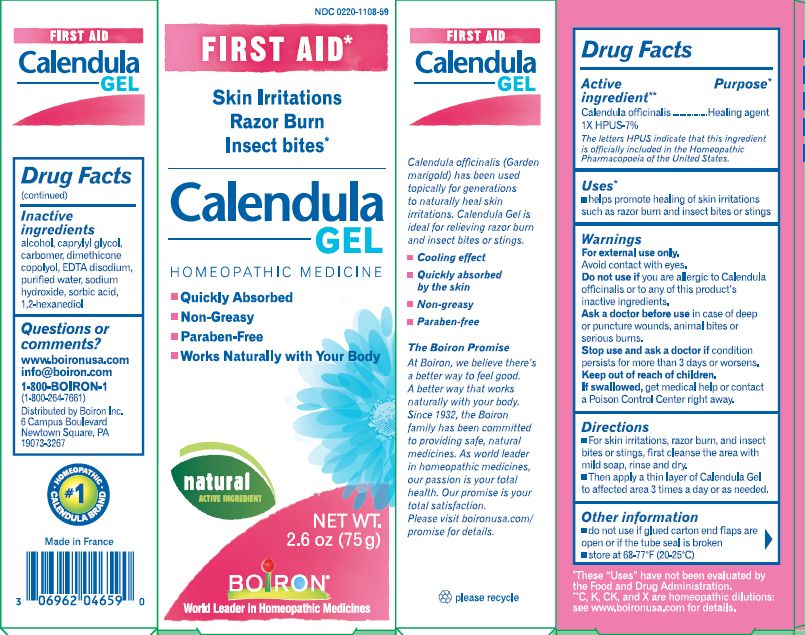 DRUG LABEL: Calendula
NDC: 0220-1108 | Form: GEL
Manufacturer: Laboratoires Boiron
Category: homeopathic | Type: HUMAN OTC DRUG LABEL
Date: 20230316

ACTIVE INGREDIENTS: CALENDULA OFFICINALIS FLOWERING TOP 1 [hp_X]/1 g
INACTIVE INGREDIENTS: CAPRYLYL GLYCOL; CARBOMER HOMOPOLYMER TYPE C; DIMETHICONE; EDETATE DISODIUM; WATER; SODIUM HYDROXIDE; SORBIC ACID; 1,2-HEXANEDIOL

Calendula Gel 2.6oz

ACTIVE INGREDIENT

Calendula officinalis 1X

INDICATIONS AND USAGE

Helps promote healing of scrapes and skin irritations.

Do not use if glued carton en flaps are open or if the tube seal is broken.

DOSAGE AND ADMINISTRATION

For scrapes and skin irritations, first cleanse the area with mild soap, rinse and dry. Then apply a thin layer of Calendula Gel to affected area 3 times a day or as needed.

INACTIVE INGREDIENT

Caprylyl glycol, carbomer, dimethicone copolyol, EDTA disodium, purified water, sodium hydroxide, sorbic acid, 1,2-hexanediol

HOW SUPPLIED

Tube 2.6 OZ (75 G)

PURPOSE

Calendula officinalis 1X ... Healing agent HPUS 7 %

STORAGE AND HANDLING

Store at 68-77O F (20-25O C)

Questions, Comments?

www.boironusa.com

info@boironusa.com

1-800-BOIRON-1 (1-800-264-7661)
Boiron Information Center
6 Campus Boulevard
Newtown Square, PA 19073-3267

ASK DOCTOR

Consult a doctor in case of deep or puncture wounds, or animal bites.

Stop use and ask doctor if condition persists for more than 3 days or worsens.

Keep out of reach of children

DRUG INTERACTIONS

Non-greasy - Paraben-Free - Quickly absorbed - Cooling effect - Works naturally with your body

WARNINGS

For external use only
Avoid contact with eyes.

If swallowed, get medical help or contact a Poison Control Center right away.